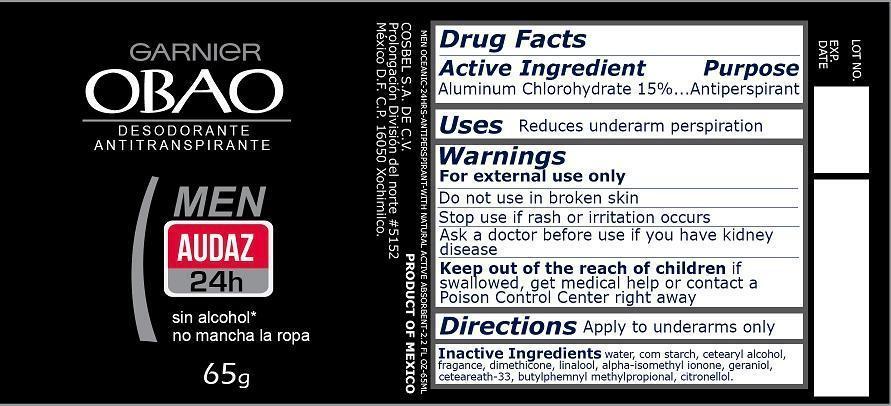 DRUG LABEL: Obao Men Audaz
NDC: 51769-888 | Form: LIQUID
Manufacturer: ALL NATURAL DYNAMICS
Category: otc | Type: HUMAN OTC DRUG LABEL
Date: 20130823

ACTIVE INGREDIENTS: ALUMINUM CHLOROHYDRATE 15 g/100 g
INACTIVE INGREDIENTS: WATER; CETOSTEARYL ALCOHOL; DIMETHICONE; ISOMETHYL-.ALPHA.-IONONE; GERANIOL; CETEARETH-33; BUTYLPHENYL METHYLPROPIONAL; .BETA.-CITRONELLOL, (R)-

Obao Men Audaz (Men Oceanic)

Active Ingredient

Aluminum Chlorohydrate 15%

Purpose

Antiperspirant

Uses

Reduces underarm perspective

Warnings

For external use only

Do not use

in broken skin

Stop use if

rash or irritation occurs

Ask a doctor

before use if you have kidney disease

Keep out of reach of children

If swallowed, get medical help or contact a Poison Control Center right away.

Directions

Apply to underarms only

Inactive Ingredients

water, corn starch, cetearyl alcohol, fragrance, dimethicone, linalool, alpha-isomethyl ionone, geraniol, ceteareath-33, butylphenyl methylpropional, citronellol.